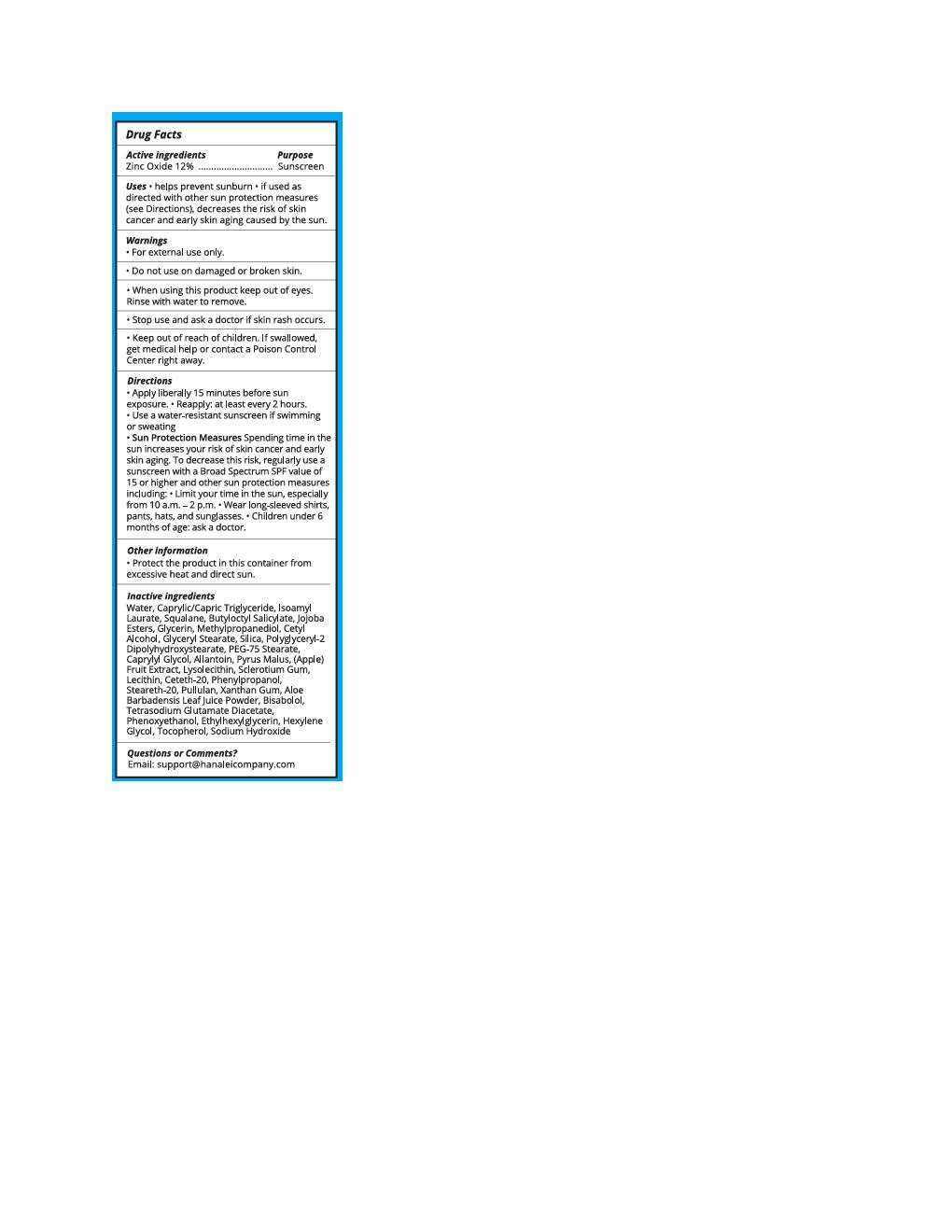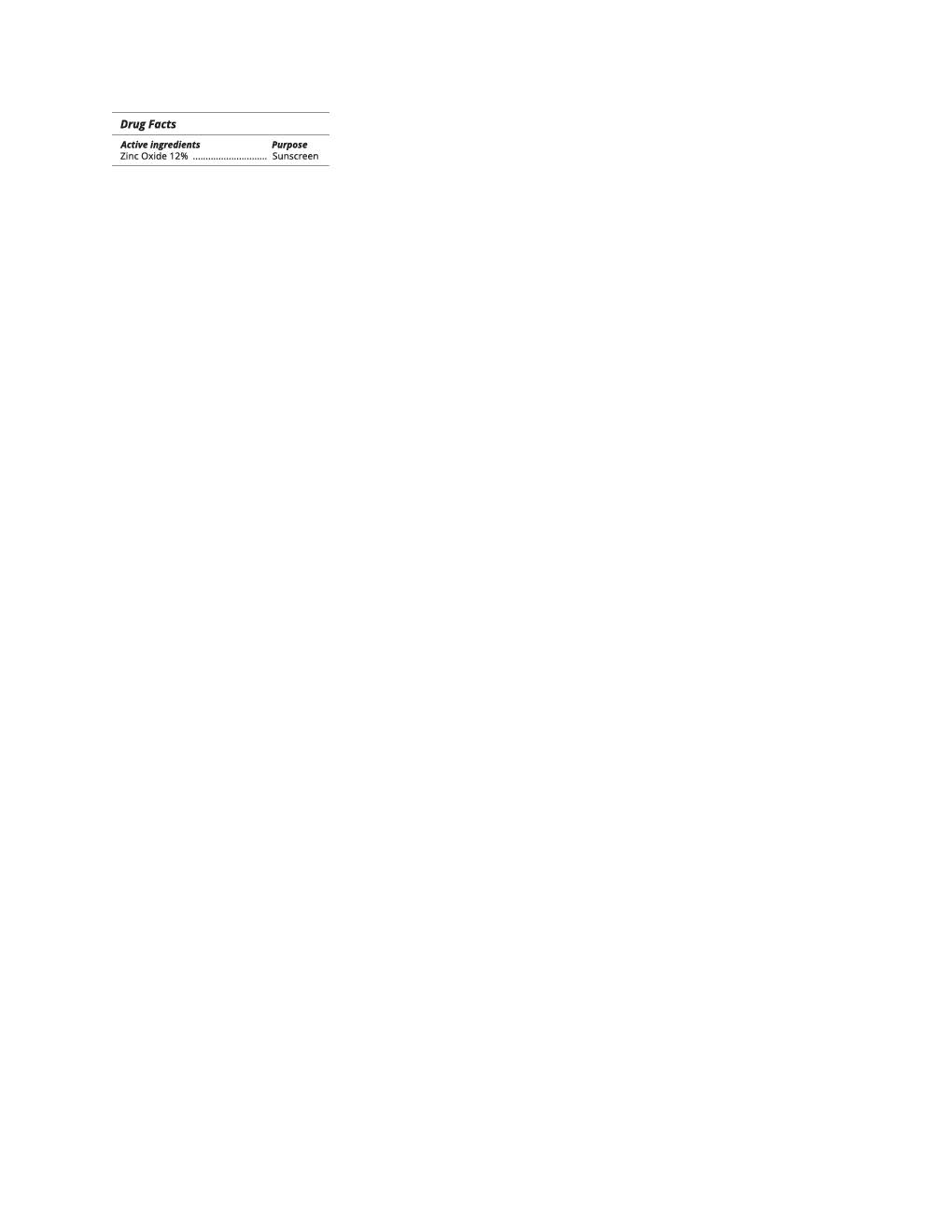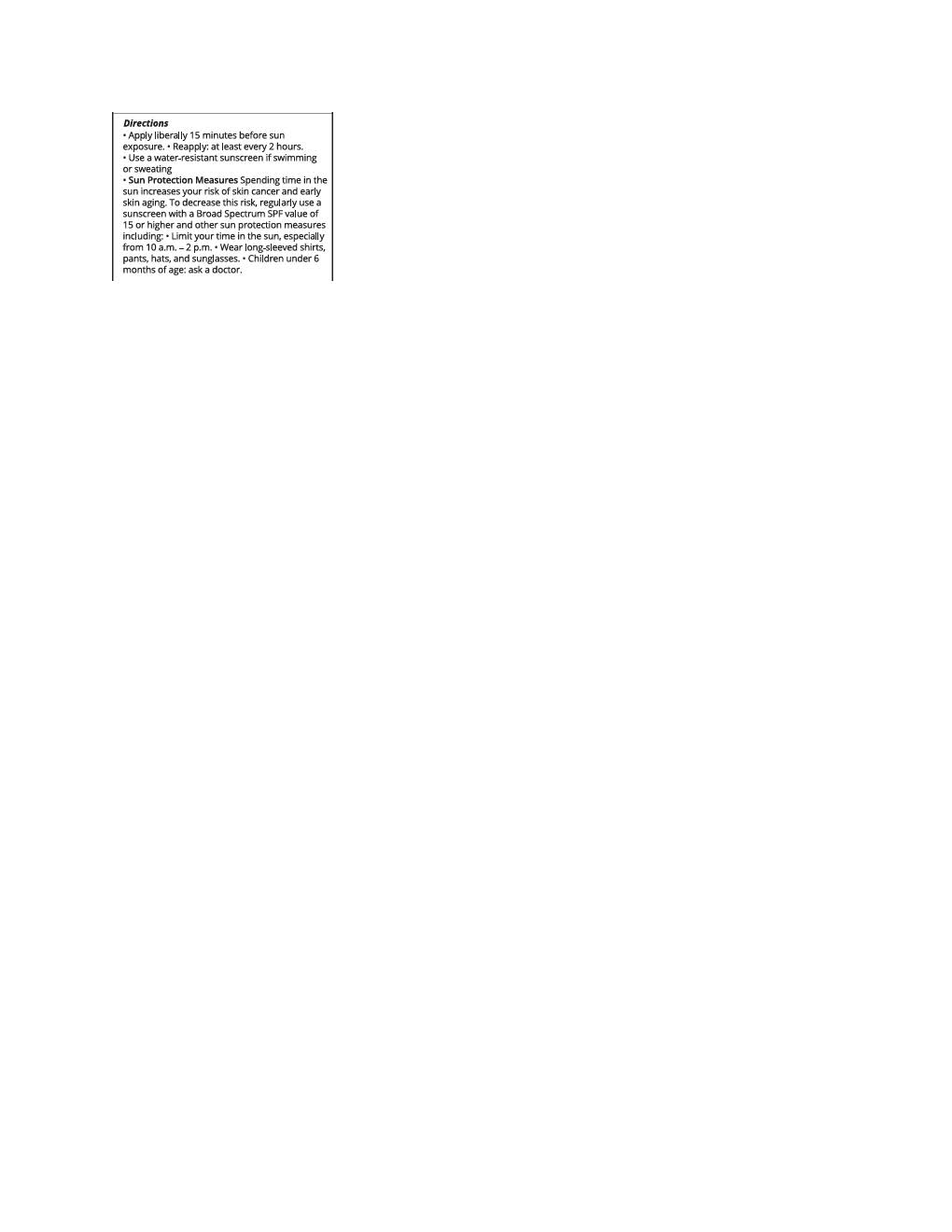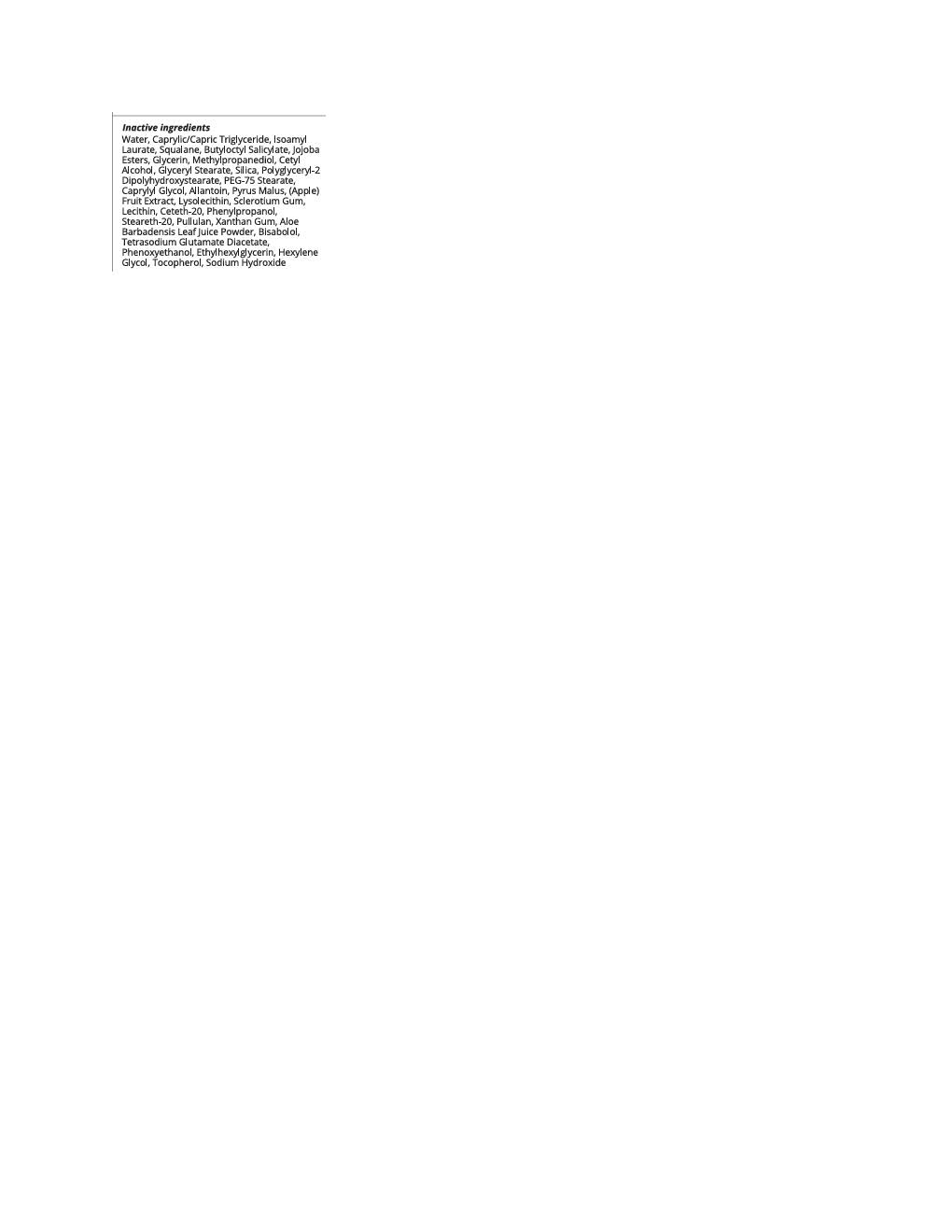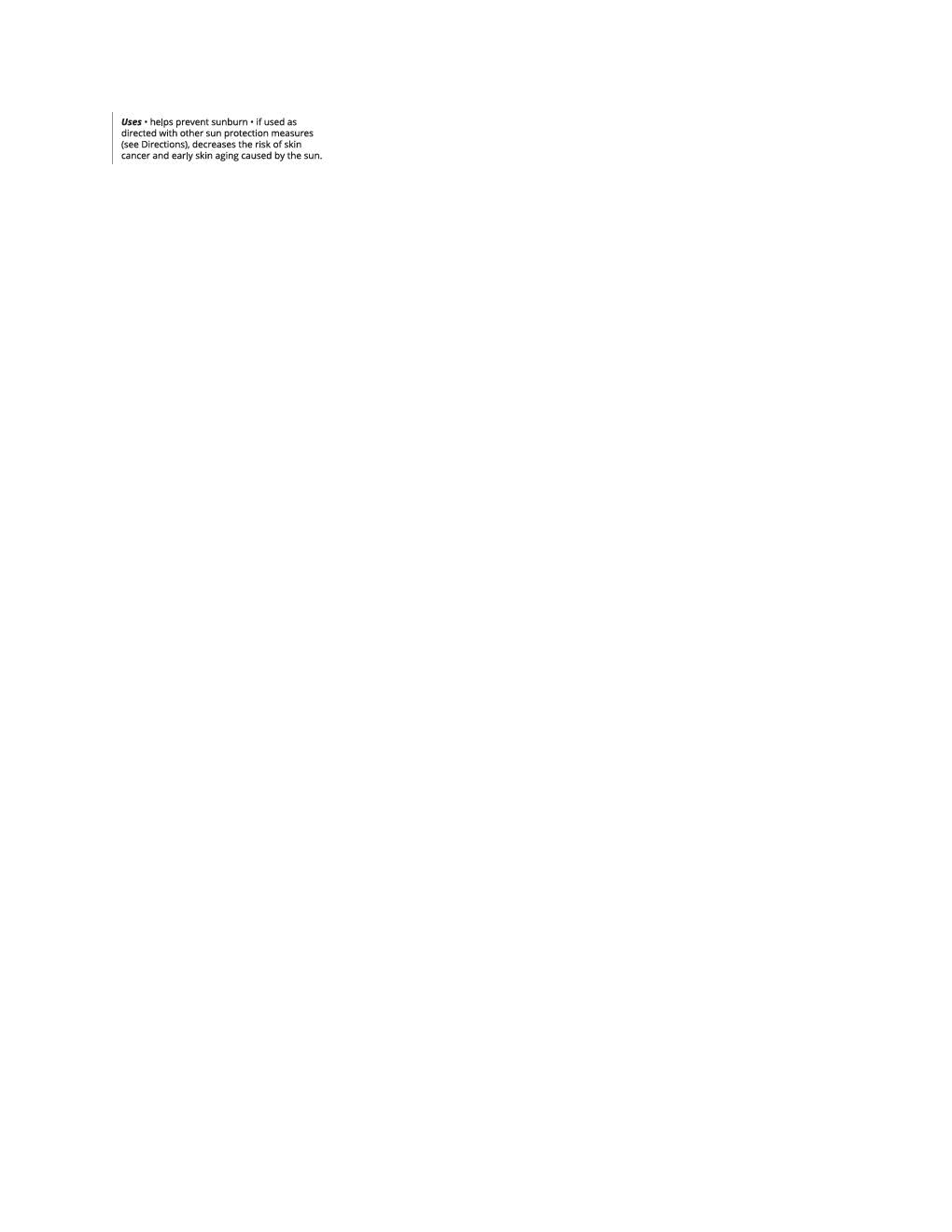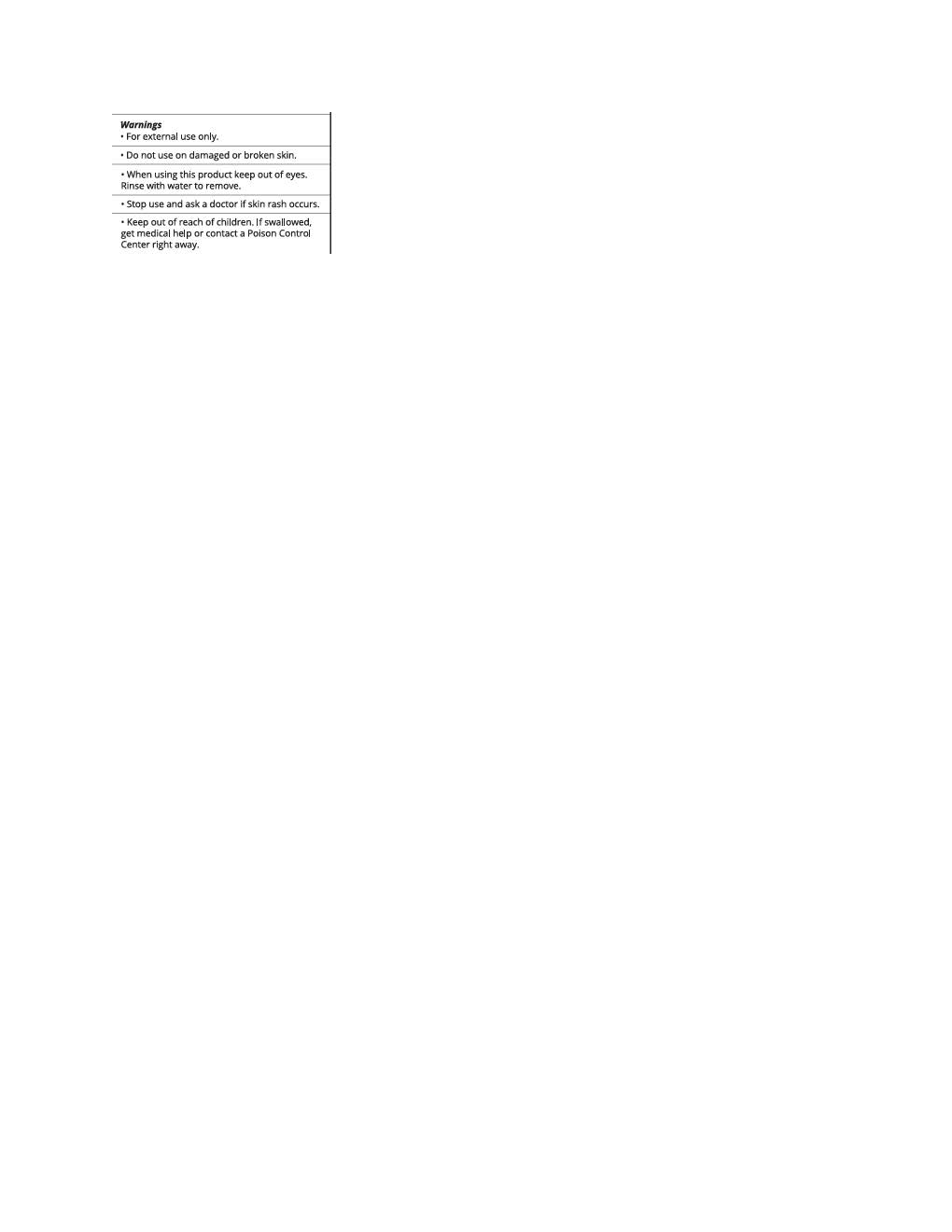 DRUG LABEL: Hanalei Face Moisturizing
NDC: 82915-2133 | Form: LOTION
Manufacturer: Hanalei Beauty Company LLC
Category: otc | Type: HUMAN OTC DRUG LABEL
Date: 20251113

ACTIVE INGREDIENTS: ZINC OXIDE 132 mg/1 mL
INACTIVE INGREDIENTS: LAVANDULA ANGUSTIFOLIA FLOWER; ALLANTOIN; TETRASODIUM GLUTAMATE DIACETATE; LECITHIN, SOYBEAN; POLYGLYCERYL-2 DIPOLYHYDROXYSTEARATE; HYDROLYZED JOJOBA ESTERS (ACID FORM); METHYLPROPANEDIOL; CAPRYLYL GLYCOL; PHENYLPROPANOL; XANTHAN GUM; ISOAMYL LAURATE; HEXYLENE GLYCOL; TOCOPHEROL; CETYL ALCOHOL; ETHYLHEXYLGLYCERIN; GLYCERIN; SILICON DIOXIDE; WATER; .ALPHA.-BISABOLOL, (+)-; BUTYLOCTYL SALICYLATE; CETETH-20; PULLULAN; SQUALANE; STEARETH-20; PHENOXYETHANOL; PEG-75 STEARATE

Hanalei Face Moisturizing